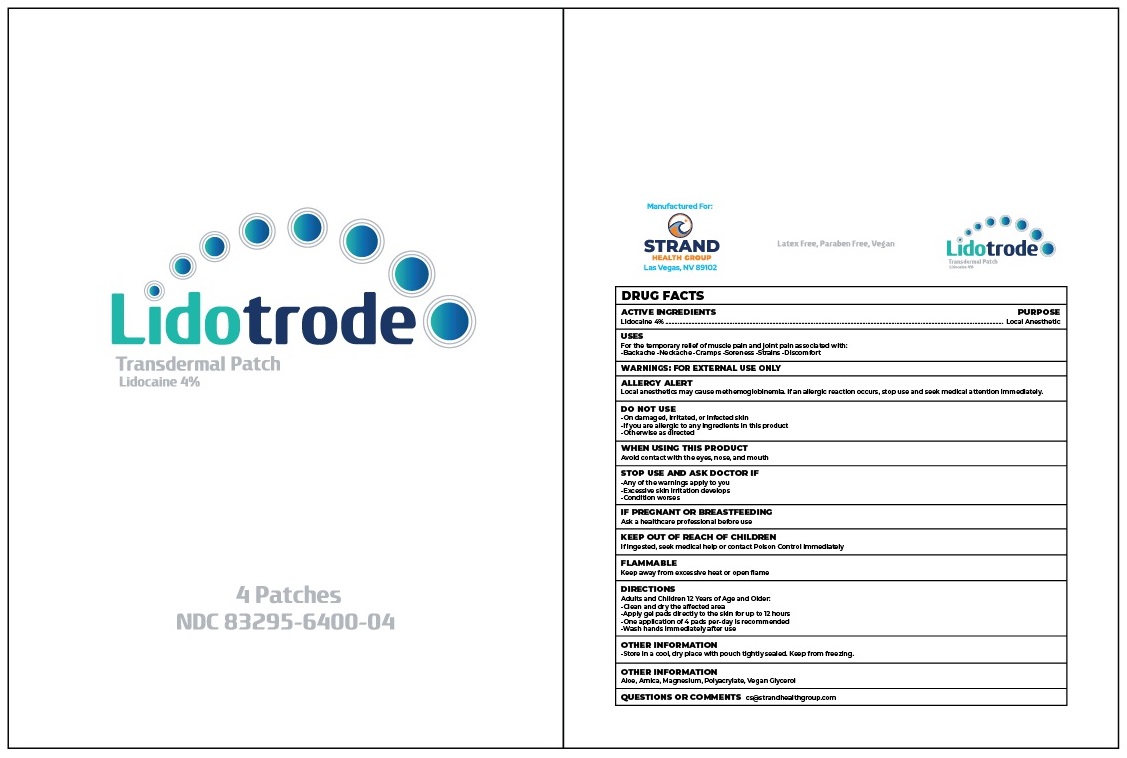 DRUG LABEL: Lidotrode
NDC: 83295-6400 | Form: PATCH
Manufacturer: Strand Health Group
Category: otc | Type: HUMAN OTC DRUG LABEL
Date: 20251218

ACTIVE INGREDIENTS: LIDOCAINE 0.04 g/1 g
INACTIVE INGREDIENTS: GLYCERIN; MAGNESIUM; WATER; ARNICA MONTANA FLOWER; POLYACRYLATE-1 CROSSPOLYMER

Lidotrode Transdermal Patch

ACTIVE INGREDIENTS

Lidocaine 4%

PURPOSE

Local Anesthetic

USES

For the temporary relief of muscle pain and joint pain associated with:

-Backache -Neckache -Cramps -Soreness -Strains -Discomfort

ALLERGY ALERT

Local anesthetics may cause methemoglobinemia. If an allergic reaction occurs, stop use and seek medical attention immediately.

DO NOT USE

-On damaged, irritated, or infected skin

-If you are allergic to any ingredients in this product

-Otherwise as directed

WHEN USING THIS PRODUCT

Avoid contact with the eyes, nose, and mouth

STOP USE AND ASK DOCTOR IF

-Any of the warnings apply to you

-Excessive skin irritation develops

-Condition worses

IF PREGNANT OR BREASTFEEDING

Ask a healthcare professional before use

KEEP OUT OF REACH OF CHILDREN

If ingested, seek medical help or contact Poison Control immediately

FLAMMABLE

Keep away from excessive heat or open flame

DIRECTIONS

Adults and Children 12 Years of Age and Older:

-Clean and dry the affected area

-Apply gel pads directly to the skin for up to 12 hours

-One application of 4 pads per-day is recommended

-Wash hands immediately after use

OTHER INFORMATION

-Store in a cool, dry place with pouch tightly sealed. Keep from freezing.

INACTIVE INGREDIENTS

Aloe, Arnica, Magnesium, Polyacrylate, Vegan Glycerol

QUESTIONS OR COMMENTS

cs@strandhealthgroup.com